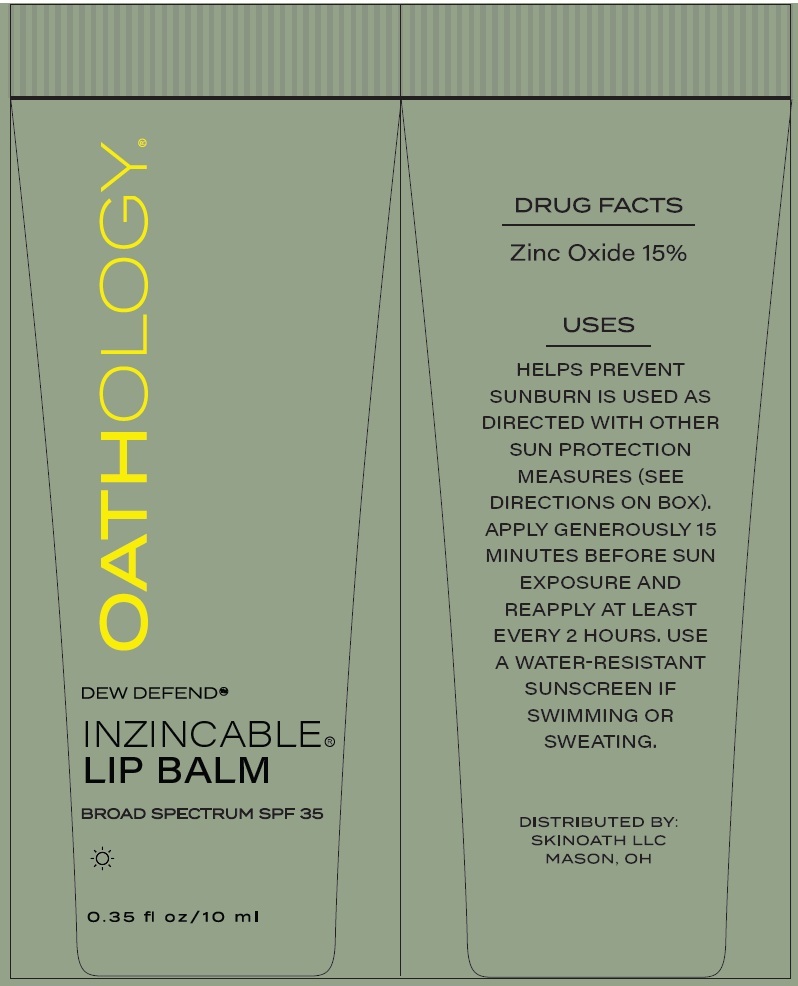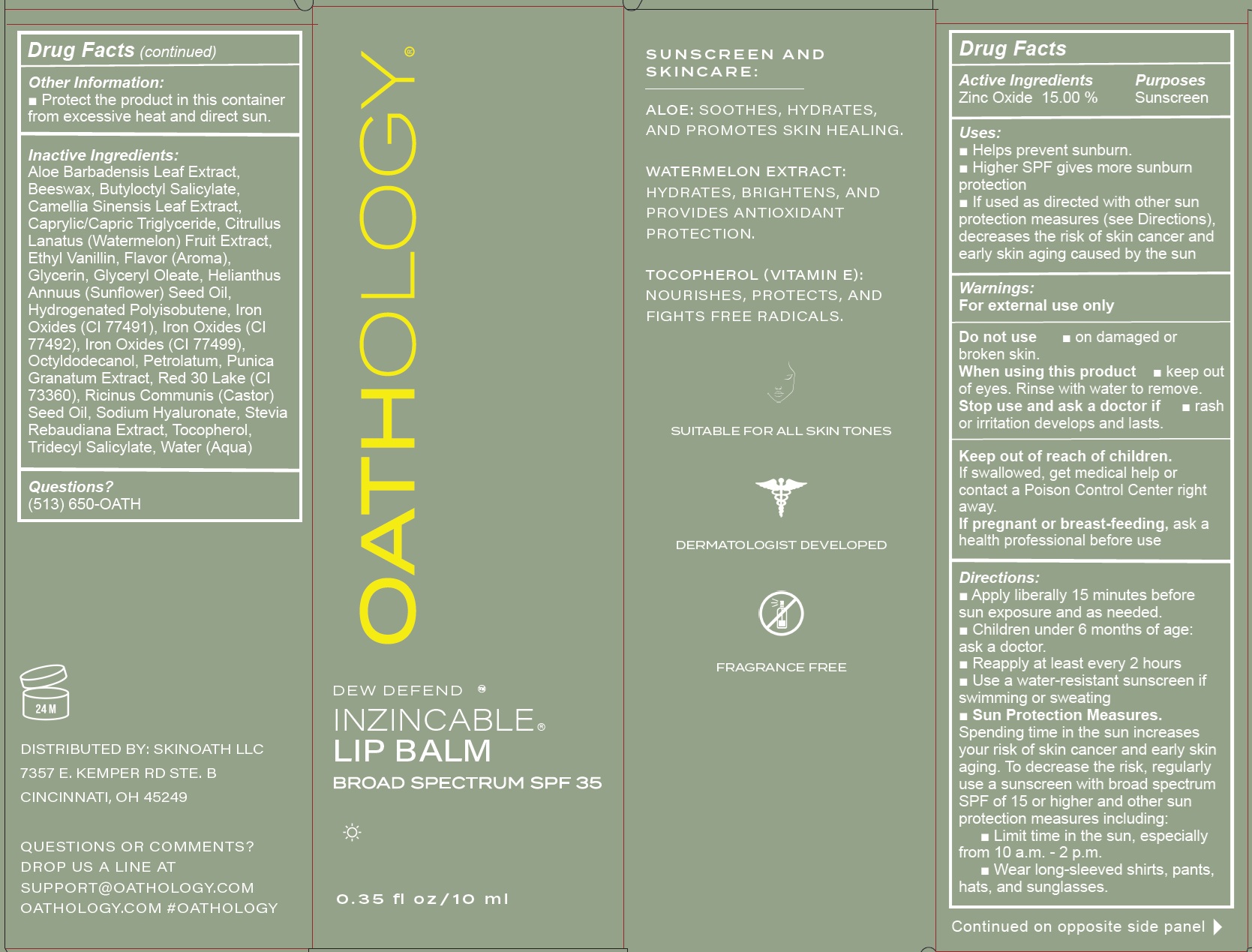 DRUG LABEL: Oathology Inzincable Lip Balm SPF 35
NDC: 85562-694 | Form: OINTMENT
Manufacturer: SKINOATH LLC
Category: otc | Type: HUMAN OTC DRUG LABEL
Date: 20250522

ACTIVE INGREDIENTS: ZINC OXIDE 150 mg/1 mL
INACTIVE INGREDIENTS: ALOE VERA LEAF; YELLOW WAX; BUTYLOCTYL SALICYLATE; GREEN TEA LEAF; MEDIUM-CHAIN TRIGLYCERIDES; WATERMELON; ETHYL VANILLIN; GLYCERIN; GLYCERYL OLEATE; SUNFLOWER OIL; FERRIC OXIDE RED; FERRIC OXIDE YELLOW; FERROSOFERRIC OXIDE; OCTYLDODECANOL; PETROLATUM; PUNICA GRANATUM ROOT BARK; D&C RED NO. 30; CASTOR OIL; HYALURONATE SODIUM; TOCOPHEROL; TRIDECYL SALICYLATE; WATER

Oathology Inzincable Lip Balm SPF 35

Active Ingredients

Zinc Oxide 15.00 %

Purposes

Sunscreen

Uses:

- Helps prevent sunburn.
- Higher SPF gives more sunburn protection
- If used as directed with other sun protection measures (see Directions), decreases the risk of skin cancer and early skin aging caused by the sun

Warnings:

For external use only

Do not use

- on damaged or broken skin.

When using this product

- keep out of eyes. Rinse with water to remove.

Stop use and ask a doctor if

- rash or irritation develops and lasts.

Keep out of reach of children.

If swallowed, get medical help or contact a Poison Control Center right away.

If pregnant or breast-feeding,

ask a health professional before use

Directions:

- Apply liberally 15 minutes before sun exposure and as needed.
- Children under 6 months of age: ask a doctor.
- Reapply at least every 2 hours
- Use a water-resistant sunscreen if swimming or sweating
- Sun Protection Measures. Spending time in the sun increases your risk of skin cancer and early skin aging. To decrease the risk, regularly use a sunscreen with broad spectrum SPF of 15 or higher and other sun protection measures including:
- Limit time in the sun, especially from 10 a.m. - 2 p.m.
- Wear long-sleeved shirts, pants, hats, and sunglasses.

Other Information:

- Protect the product in this container from excessive heat and direct sun.

Inactive Ingredients:

Aloe Barbadensis Leaf Extract, Beeswax, Butyloctyl Salicylate, Camellia Sinensis Leaf Extract, Caprylic/Capric Triglyceride, Citrullus Lanatus (Watermelon) Fruit Extract, Ethyl Vanillin, Flavor (Aroma), Glycerin, Glyceryl Oleate, Helianthus Annuus (Sunflower) Seed Oil, Hydrogenated Polyisobutene, Iron Oxides (CI 77491), Iron Oxides (CI 77492), Iron Oxides (CI 77499), Octyldodecanol, Petrolatum, Punica Granatum Extract, Red 30 Lake (CI 73360), Ricinus Communis (Castor) Seed Oil, Sodium Hyaluronate, Stevia Rebaudiana Extract, Tocopherol, Tridecyl Salicylate, Water (Aqua)

Questions?

(513) 650-OATH